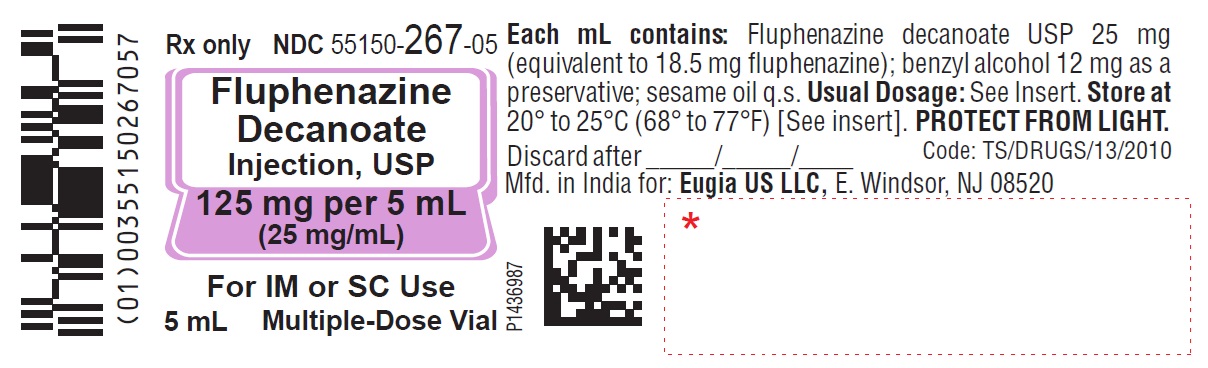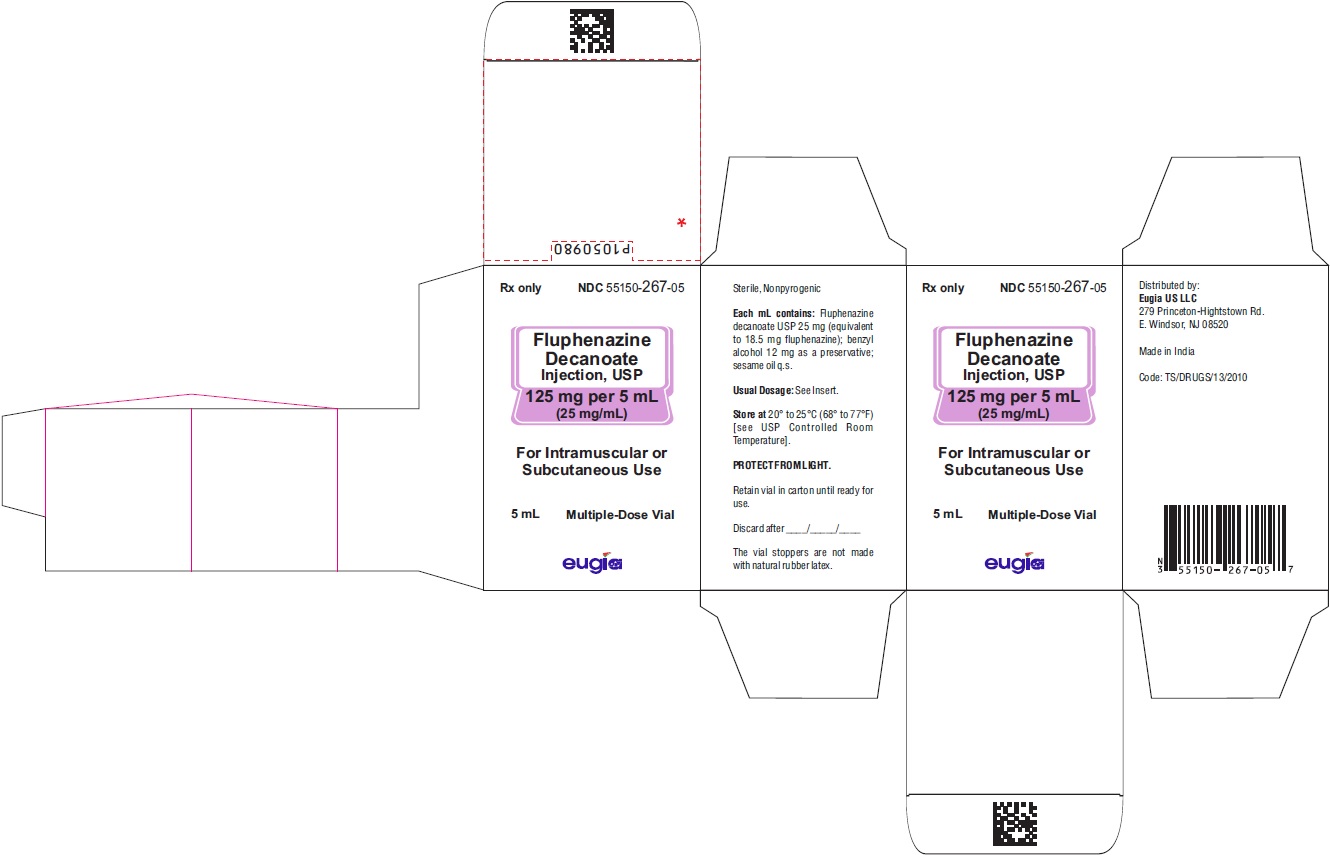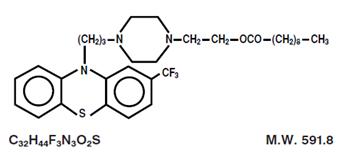 DRUG LABEL: FLUPHENAZINE DECANOATE
NDC: 55150-267 | Form: INJECTION, SOLUTION
Manufacturer: Eugia US LLC
Category: prescription | Type: Human Prescription Drug Label
Date: 20251107

ACTIVE INGREDIENTS: FLUPHENAZINE DECANOATE 125 mg/5 mL
INACTIVE INGREDIENTS: BENZYL ALCOHOL; SESAME OIL

Fluphenazine Decanoate Injection, USP
Rx only

WARNING

Increased Mortality in Elderly Patients with Dementia-Related Psychosis — Elderly patients with dementia-related psychosis treated with antipsychotic drugs are at an increased risk of death. Analyses of seventeen placebo-controlled trials (modal duration of 10 weeks), largely in patients taking atypical antipsychotic drugs, revealed a risk of death in drug treated patients of between 1.6 to 1.7 times the risk of death in placebo-treated patients. Over the course of a typical 10-week controlled trial, the rate of death in drug-treated patients was about 4.5%, compared to a rate of about 2.6% in the placebo group. Although the causes of death were varied, most of the deaths appeared to be either cardiovascular (e.g., heart failure, sudden death) or infectious (e.g., pneumonia) in nature. Observational studies suggest that, similar to atypical antipsychotic drugs, treatment with conventional antipsychotic drugs may increase mortality. The extent to which the findings of increased mortality in observational studies may be attributed to the antipsychotic drug as opposed to some characteristic(s) of the patients is not clear. Fluphenazine Decanoate Injection is not approved for the treatment of patients with dementia-related psychosis (see WARNINGS).

DESCRIPTION

Fluphenazine decanoate is the decanoate ester of a trifluoromethyl phenothiazine derivative. It is a highly potent behavior modifier with a markedly extended duration of effect and has the following structural formula:
Fluphenazine Decanoate USP is a yellow solid.
Fluphenazine Decanoate Injection, USP is available as a sterile, clear, pale yellow solution for intramuscular (IM) or subcutaneous (SC) use providing 25 mg fluphenazine decanoate USP (equivalent to 18.5 mg fluphenazine) per mL in a sesame oil vehicle with 12 mg benzyl alcohol as a preservative.

CLINICAL PHARMACOLOGY

The basic effects of fluphenazine decanoate appear to be no different from those of fluphenazine hydrochloride, with the exception of duration of action. The esterification of fluphenazine markedly prolongs the drug’s duration of effect without unduly attenuating its beneficial action.
Fluphenazine decanoate has activity at all levels of the central nervous system (CNS) as well as on multiple organ systems. The mechanism whereby its therapeutic action is exerted is unknown.
Fluphenazine differs from other phenothiazine derivatives in several respects: it is more potent on a milligram basis, it has less potentiating effect on CNS depressants and anesthetics than do some of the phenothiazines and appears to be less sedating, and it is less likely than some of the older phenothiazines to produce hypotension (nevertheless, appropriate cautions should be observed, see PRECAUTIONS and ADVERSE REACTIONS).

INDICATIONS AND USAGE

Fluphenazine Decanoate Injection is a long-acting parenteral antipsychotic drug intended for use in the management of patients requiring prolonged parenteral neuroleptic therapy (e.g., chronic schizophrenics).
Fluphenazine Decanoate Injection has not been shown effective in the management of behavioral complications in patients with mental retardation.

CONTRAINDICATIONS

Phenothiazines are contraindicated in patients with suspected or established subcortical brain damage.
Phenothiazine compounds should not be used in patients receiving large doses of hypnotics.
Fluphenazine Decanoate Injection is contraindicated in comatose or severely depressed states.
The presence of blood dyscrasia or liver damage precludes the use of fluphenazine decanoate.
Fluphenazine Decanoate Injection is not intended for use in children under 12 years of age.
Fluphenazine Decanoate Injection is contraindicated in patients who have shown hypersensitivity to fluphenazine; cross-sensitivity to phenothiazine derivatives may occur.

WARNINGS

Increased Mortality in Elderly Patients with Dementia-Related Psychosis
Elderly patients with dementia-related psychosis treated with antipsychotic drugs are at an increased risk of death. Fluphenazine Decanoate Injection is not approved for the treatment of patients with dementia-related psychosis (see BOXED WARNING).
Tardive Dyskinesia

Tardive dyskinesia, a syndrome consisting of potentially irreversible, involuntary, dyskinetic movements, may develop in patients treated with neuroleptic (antipsychotic) drugs. Although the prevalence of the syndrome appears to be highest among the elderly, especially elderly women, it is impossible to rely upon prevalence estimates to predict, at the inception of neuroleptic treatment, which patients are likely to develop the syndrome. Whether neuroleptic drug products differ in their potential to cause tardive dyskinesia is unknown.
Both the risk of developing the syndrome and the likelihood that it will become irreversible are believed to increase as the duration of treatment and the total cumulative dose of neuroleptic drugs administered to the patient increase. However, the syndrome can develop, although much less commonly, after relatively brief treatment periods at low doses.
There is no known treatment for established cases of tardive dyskinesia, although the syndrome may remit, partially or completely, if neuroleptic treatment is withdrawn. Neuroleptic treatment, itself, however, may suppress (or partially suppress) the signs and symptoms of the syndrome and thereby may possibly mask the underlying disease process. The effect that symptomatic suppression has upon the long-term course of the syndrome is unknown.
Given these considerations, neuroleptics should be prescribed in a manner that is most likely to minimize the occurrence of tardive dyskinesia. Chronic neuroleptic treatment should generally be reserved for patients who suffer from a chronic illness that, 1) is known to respond to neuroleptic drugs, and, 2) for whom alternative equally effective, but potentially less harmful treatments are not available or appropriate. In patients who do require chronic treatment, the smallest dose and the shortest duration of treatment producing a satisfactory clinical response should be sought. The need for continued treatment should be reassessed periodically.
If signs and symptoms of tardive dyskinesia appear in a patient on neuroleptics, drug discontinuation should be considered. However, some patients may require treatment despite the presence of the syndrome.
(For further information about the description of tardive dyskinesia and its clinical detection, please refer to the sections on PRECAUTIONS, Information for Patients, and ADVERSE REACTIONS, Tardive Dyskinesia.)

Neuroleptic Malignant Syndrome (NMS)

A potentially fatal symptom complex sometimes referred to as Neuroleptic Malignant Syndrome (NMS) has been reported in association with antipsychotic drugs. Clinical manifestations of NMS are hyperpyrexia, muscle rigidity, altered mental status and evidence of autonomic instability (irregular pulse or blood pressure, tachycardia, diaphoresis, and cardiac dysrhythmias).
The diagnostic evaluation of patients with this syndrome is complicated. In arriving at a diagnosis, it is important to identify cases where the clinical presentation includes both serious medical illness (e.g., pneumonia, systemic infection, etc.) and untreated or inadequately treated extrapyramidal signs and symptoms (EPS). Other important considerations in the differential diagnosis include central anticholinergic toxicity, heat stroke, drug fever and primary CNS pathology.
The management of NMS should include 1) immediate discontinuation of antipsychotic drugs and other drugs not essential to concurrent therapy, 2) intensive symptomatic treatment and medical monitoring, and 3) treatment of any concomitant serious medical problems for which specific treatments are available. There is no general agreement about specific pharmacological treatment regimens for uncomplicated NMS.
If a patient requires antipsychotic drug treatment after recovery from NMS, the potential reintroduction of drug therapy should be carefully considered. The patient should be carefully monitored, since recurrences of NMS have been reported.
Falls
Fluphenazine Decanoate Injection may cause somnolence, postural hypotension, motor and sensory instability, which may lead to falls and, consequently, fractures or other injuries. For patients with diseases, conditions, or medications that could exacerbate these effects, complete fall risk assessments when initiating antipsychotic treatment and recurrently for patients on long-term antipsychotic therapy.
Others
The use of this drug may impair the mental and physical abilities required for driving a car or operating heavy machinery.
Physicians should be alert to the possibility that severe adverse reactions may occur which require immediate medical attention.
Potentiation of the effects of alcohol may occur with the use of this drug.
Since there is no adequate experience in children who have received this drug, safety and efficacy in children have not been established.
Usage In Pregnancy
The safety for the use of this drug during pregnancy has not been established; therefore, the possible hazards should be weighed against the potential benefits when administering this drug to pregnant patients.

PRECAUTIONS

General
Because of the possibility of cross-sensitivity, fluphenazine decanoate should be used cautiously in patients who have developed cholestatic jaundice, dermatoses, or other allergic reactions to phenothiazine derivatives.
Psychotic patients on large doses of a phenothiazine drug who are undergoing surgery should be watched carefully for possible hypotensive phenomena. Moreover, it should be remembered that reduced amounts of anesthetics or CNS depressants may be necessary.
The effects of atropine may be potentiated in some patients receiving fluphenazine because of added anticholinergic effects.
Fluphenazine decanoate should be used cautiously in patients exposed to extreme heat or phosphorus insecticides.
The preparation should be used with caution in patients with a history of convulsive disorders, since grand mal convulsions have been known to occur.
Use with caution in patients with special medical disorders such as mitral insufficiency or other cardiovascular disease and pheochromocytoma.
The possibility of liver damage, pigmentary retinopathy, lenticular and corneal deposits, and development of irreversible dyskinesia should be remembered when patients are on prolonged therapy.
Outside state hospitals or other psychiatric institutions, fluphenazine decanoate should be administered under the direction of a physician experienced in the clinical use of psychotropic drugs, particularly phenothiazine derivatives. Furthermore, facilities should be available for periodic checking of hepatic function, renal function, and the blood picture. Renal function of patients on long-term therapy should be monitored; if blood urea nitrogen (BUN) becomes abnormal, treatment should be discontinued.
As with any phenothiazine, the physician should be alert to the possible development of “silent pneumonias” in patients under treatment with fluphenazine decanoate.

Neuroleptic drugs elevate prolactin levels; the elevation persists during chronic administration. Tissue culture experiments indicate that approximately one-third of human breast cancers are prolactin dependent in vitro, a factor of potential importance if the prescription of these drugs is contemplated in a patient with a previously detected breast cancer. Although disturbances such as galactorrhea, amenorrhea, gynecomastia, and impotence have been reported, the clinical significance of elevated serum prolactin levels is unknown for most patients. An increase in mammary neoplasms has been found in rodents after chronic administration of neuroleptic drugs. Published epidemiologic studies have shown inconsistent results when exploring the association between hyperprolactinemia and breast cancer.
Pregnancy
Non-teratogenic Effects
Neonates exposed to antipsychotic drugs, during the third trimester of pregnancy are at risk for extrapyramidal and/or withdrawal symptoms following delivery. There have been reports of agitation, hypertonia, hypotonia, tremor, somnolence, respiratory distress and feeding disorder in these neonates. These complications have varied in severity; while in some cases symptoms have been self-limited, in other cases neonates have required intensive care unit support and prolonged hospitalization.
Fluphenazine Decanoate should be used during pregnancy only if the potential benefit justifies the potential risk to the fetus.
Leukopenia, Neutropenia and Agranulocytosis
In clinical trial and postmarketing experience, events of leukopenia/neutropenia and agranulocytosis have been reported temporally related to antipsychotic agents.
Possible risk factors for leukopenia/neutropenia include pre-existing low white blood cell count (WBC) and history of drug induced leukopenia/neutropenia. Patients with a pre-existing low WBC or a history of drug induced leukopenia/neutropenia should have their complete blood count (CBC) monitored frequently during the first few months of therapy and should discontinue Fluphenazine Decanoate Injection at the first sign of a decline in WBC in the absence of other causative factors.
Patients with neutropenia should be carefully monitored for fever or other symptoms or signs of infection and treated promptly if such symptoms or signs occur. Patients with severe neutropenia (absolute neutrophil count <1,000/mm^3) should discontinue Fluphenazine Decanoate Injection and have their WBC followed until recovery.
Information for Patients
Given the likelihood that a substantial proportion of patients exposed chronically to neuroleptics will develop tardive dyskinesia, it is advised that all patients in whom chronic use is contemplated be given, if possible, full information about this risk. The decision to inform patients and/or their guardians must obviously take into account the clinical circumstances and the competency of the patient to understand the information provided.

ADVERSE REACTIONS

Central Nervous System
The side effects most frequently reported with phenothiazine compounds are extrapyramidal symptoms including pseudoparkinsonism, dystonia, dyskinesia, akathisia, oculogyric crises, opisthotonos, and hyperreflexia. Muscle rigidity sometimes accompanied by hyperthermia has been reported following use of fluphenazine decanoate. Most often these extrapyramidal symptoms are reversible; however, they may be persistent (see below). The frequency of such reactions is related in part to chemical structure: one can expect a higher incidence with fluphenazine decanoate than with less potent piperazine derivatives or with straight-chain phenothiazines such as chlorpromazine. With any given phenothiazine derivative, the incidence and severity of such reactions depend more on individual patient sensitivity than on other factors, but dosage level and patient age are also determinants.
Extrapyramidal reactions may be alarming, and the patient should be forewarned and reassured. These reactions can usually be controlled by administration of antiparkinsonian drugs such as Benztropine Mesylate or Intravenous Caffeine and Sodium Benzoate Injection, and by subsequent reduction in dosage.
Tardive Dyskinesia
See WARNINGS. The syndrome is characterized by involuntary choreoathetoid movements which variously involve the tongue, face, mouth, lips, or jaw (e.g., protrusion of the tongue, puffing of cheeks, puckering of the mouth, chewing movements), trunk and extremities. The severity of the syndrome and the degree of impairment produced vary widely.
The syndrome may become clinically recognizable either during treatment, upon dosage reduction, or upon withdrawal of treatment. Early detection of tardive dyskinesia is important. To increase the likelihood of detecting the syndrome at the earliest possible time, the dosage of the neuroleptic drug should be reduced periodically (if clinically possible) and the patient observed for signs of the disorder. This maneuver is critical, since neuroleptic drugs may mask the signs of the syndrome.
Other CNS Effects
Occurrences of neuroleptic malignant syndrome (NMS) have been reported in patients on neuroleptic therapy (see WARNINGS, Neuroleptic Malignant Syndrome); leukocytosis, elevated CPK, liver function abnormalities, and acute renal failure may also occur with NMS.
Drowsiness or lethargy, if they occur, may necessitate a reduction in dosage; the induction of a catatonic-like state has been known to occur with dosages of fluphenazine far in excess of the recommended amounts. As with other phenothiazine compounds, reactivation or aggravation of psychotic processes may be encountered.
Phenothiazine derivatives have been known to cause, in some patients, restlessness, excitement, or bizarre dreams.
Autonomic Nervous System
Hypertension and fluctuations in blood pressure have been reported with fluphenazine.
Hypotension has rarely presented a problem with fluphenazine. However, patients with pheochromocytoma, cerebral, vascular or renal insufficiency, or a severe cardiac reserve deficiency such as mitral insufficiency appear to be particularly prone to hypotensive reactions with phenothiazine compounds, and should therefore be observed closely when the drug is administered. If severe hypotension should occur, supportive measures including the use of intravenous vasopressor drugs should be instituted immediately. Norepinephrine Bitartrate Injection is the most suitable drug for this purpose: epinephrine should not be used since phenothiazine derivatives have been found to reverse its action, resulting in a further lowering of blood pressure.
Autonomic reactions including nausea and loss of appetite, salivation, polyuria, perspiration, dry mouth, headache, and constipation may occur. Autonomic effects can usually be controlled by reducing or temporarily discontinuing dosage.
In some patients, phenothiazine derivatives have caused blurred vision, glaucoma, bladder paralysis, fecal impaction, paralytic ileus, tachycardia, or nasal congestion.
Metabolic and Endocrine
Weight change, peripheral edema, abnormal lactation, gynecomastia, menstrual irregularities, false results on pregnancy tests, impotency in men and increased libido in women have all been known to occur in some patients on phenothiazine therapy.
Allergic Reactions
Skin disorders such as itching, erythema, urticaria, seborrhea, photosensitivity, eczema and even exfoliative dermatitis have been reported with phenothiazine derivatives. The possibility of anaphylactoid reactions occurring in some patients should be borne in mind.
Hematologic
Routine blood counts are advisable during therapy since blood dyscrasias including leukopenia, agranulocytosis, thrombocytopenic or nonthrombocytopenic purpura, eosinophilia, and pancytopenia have been observed with phenothiazine derivatives. Furthermore, if any soreness of the mouth, gums, or throat, or any symptoms of upper respiratory infection occur and confirmatory leukocyte count indicates cellular depression, therapy should be discontinued and other appropriate measures instituted immediately.
Hepatic
Liver damage as manifested by cholestatic jaundice may be encountered, particularly during the first months of therapy; treatment should be discontinued if this occurs. An increase in cephalin flocculation, sometimes accompanied by alterations in other liver function tests, has been reported in patients receiving the enanthate ester of fluphenazine (a closely related compound) who have had no clinical evidence of liver damage.
Others
Sudden, unexpected and unexplained deaths have been reported in hospitalized psychotic patients receiving phenothiazines. Previous brain damage or seizures may be predisposing factors; high doses should be avoided in known seizure patients. Several patients have shown sudden flare-ups of psychotic behavior patterns shortly before death. Autopsy findings have usually revealed acute fulminating pneumonia or pneumonitis, aspiration of gastric contents, or intramyocardial lesions.
Although this is not a general feature of fluphenazine, potentiation of CNS depressants (opiates, analgesics, antihistamines, barbiturates, alcohol) may occur.
The following adverse reactions have also occurred with phenothiazine derivatives: Systemic lupus erythematosus-like syndrome, hypotension severe enough to cause fatal cardiac arrest, altered electrocardiographic and electroencephalographic tracings, altered cerebrospinal fluid proteins, cerebral edema, asthma, laryngeal edema, and angioneurotic edema; with long-term use, skin pigmentation, and lenticular and corneal opacities.
Injections of fluphenazine decanoate are extremely well tolerated, local tissue reactions occurring only rarely.

DOSAGE AND ADMINISTRATION

Fluphenazine Decanoate Injection may be given IM or SC. A dry syringe and needle of at least 21 gauge should be used. Use of a wet needle or syringe may cause the solution to become cloudy.
To begin therapy with Fluphenazine Decanoate Injection, the following regimens are suggested:
For most patients, a dose of 12.5 to 25 mg (0.5 to 1 mL) may be given to initiate therapy. The onset of action generally appears between 24 and 72 hours after injection and the effects of the drug on psychotic symptoms becomes significant within 48 to 96 hours. Subsequent injections and the dosage interval are determined in accordance with the patient’s response. When administered as maintenance therapy, a single injection may be effective in controlling schizophrenic symptoms up to four weeks or longer. The response to a single dose has been found to last as long as six weeks in a few patients on maintenance therapy.
It may be advisable that patients who have no history of taking phenothiazines should be treated initially with a shorter-acting form of fluphenazine before administering the decanoate to determine the patient’s response to fluphenazine and to establish appropriate dosage. For psychotic patients who have been stabilized on a fixed daily dosage of Fluphenazine Hydrochloride Tablets, USP or Fluphenazine Hydrochloride Elixir, USP conversion of therapy from these short-acting oral forms to the long-acting Fluphenazine Decanoate Injection may be indicated.
Appropriate dosage of Fluphenazine Decanoate Injection should be individualized for each patient and responses carefully monitored. No precise formula can be given to convert to use of Fluphenazine Decanoate Injection; however, a controlled multicentered study,* in patients receiving oral doses from 5 to 60 mg fluphenazine hydrochloride daily, showed that 20 mg fluphenazine hydrochloride daily was equivalent to 25 mg (1 mL) of Fluphenazine Decanoate Injection every three weeks. This represents an approximate conversion ratio of 12.5 mg (0.5 mL) of decanoate every three weeks for every 10 mg of fluphenazine hydrochloride daily.
Once conversion to Fluphenazine Decanoate Injection is made, careful clinical monitoring of the patient and appropriate dosage adjustment should be made at the time of each injection.
Severely agitated patients may be treated initially with a rapid-acting phenothiazine compound such as Fluphenazine Hydrochloride Injection—see Package Insert accompanying that product for complete information. When acute symptoms have subsided, 25 mg (1 mL) of Fluphenazine Decanoate Injection may be administered; subsequent dosage is adjusted as necessary.
“Poor risk” patients (those with known hypersensitivity to phenothiazines, or with disorders that predispose to undue reactions): Therapy may be initiated cautiously with oral or parenteral fluphenazine hydrochloride (see Package Inserts accompanying these products for complete information). When the pharmacologic effects and an appropriate dosage are apparent, an equivalent dose of fluphenazine decanoate may be administered. Subsequent dosage adjustments are made in accordance with the response of the patient.
The optimal amount of the drug and the frequency of administration must be determined for each patient, since dosage requirements have been found to vary with clinical circumstances as well as with individual response to the drug.
Dosage should not exceed 100 mg. If doses greater than 50 mg are deemed necessary, the next dose and succeeding doses should be increased cautiously in increments of 12.5 mg.
Parenteral drug products should be inspected visually for particulate matter and discoloration prior to administration, whenever solution and container permit.

HOW SUPPLIED

Fluphenazine Decanoate Injection, USP is a sterile, clear, pale yellow solution and is supplied as follows:
125 mg per 5 mL (25 mg/mL)
5 mL Multiple-Dose Vials
Packaged Individually NDC 55150-267-05
Store at 20° to 25°C (68° to 77°F) [see USP Controlled Room Temperature].
Protect from light (keep in outer carton).
The vial stoppers are not made with natural rubber latex.
* Schooler, N.R.: The Initiation of Long-Term Pharmacotherapy in Schizophrenia: Dosage and Side Effect Comparisons between Oral and Depot Fluphenazine Pharmakopsych. 9:159-169, 1976.
Distributed by:
Eugia US LLC
279 Princeton-Hightstown Rd.
E. Windsor, NJ 08520
Manufactured by:
Eugia Pharma Specialities Limited
Hyderabad - 500032
India
Revised: November 2024

PACKAGE LABEL-PRINCIPAL DISPLAY PANEL - 125 mg per 5 mL (25 mg/mL) - Container Label

Rx only NDC 55150-267-05
Fluphenazine
Decanoate
Injection, USP
125 mg per 5 mL
(25 mg/mL)
For IM or SC Use
5 mL Multiple-Dose Vial

PACKAGE LABEL-PRINCIPAL DISPLAY PANEL - 125 mg per 5 mL (25 mg/mL) - Container-Carton (1 Vial)

Rx only NDC 55150-267-05
Fluphenazine
Decanoate
Injection, USP
125 mg per 5 mL
(25 mg/mL)
For Intramuscular or
Subcutaneous Use
5 mL Multiple-Dose Vial
eugia